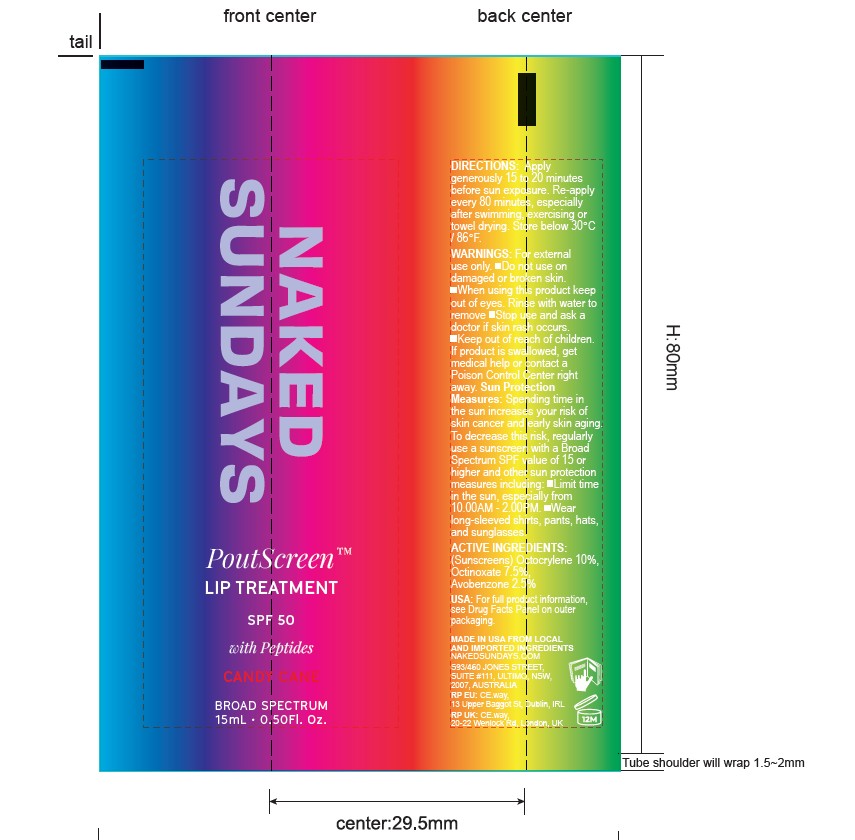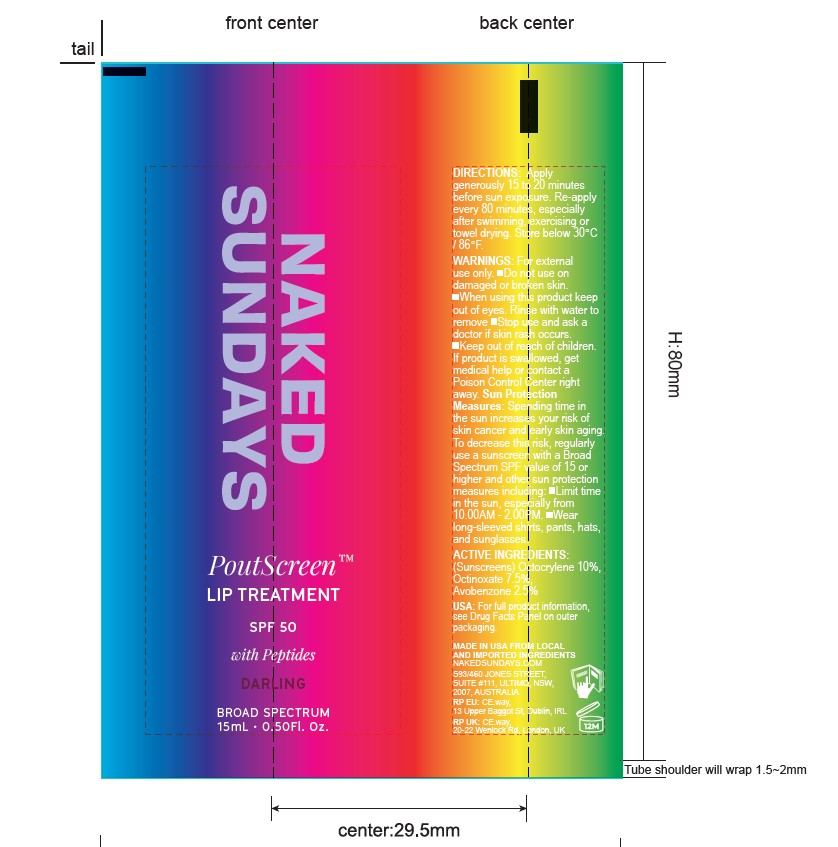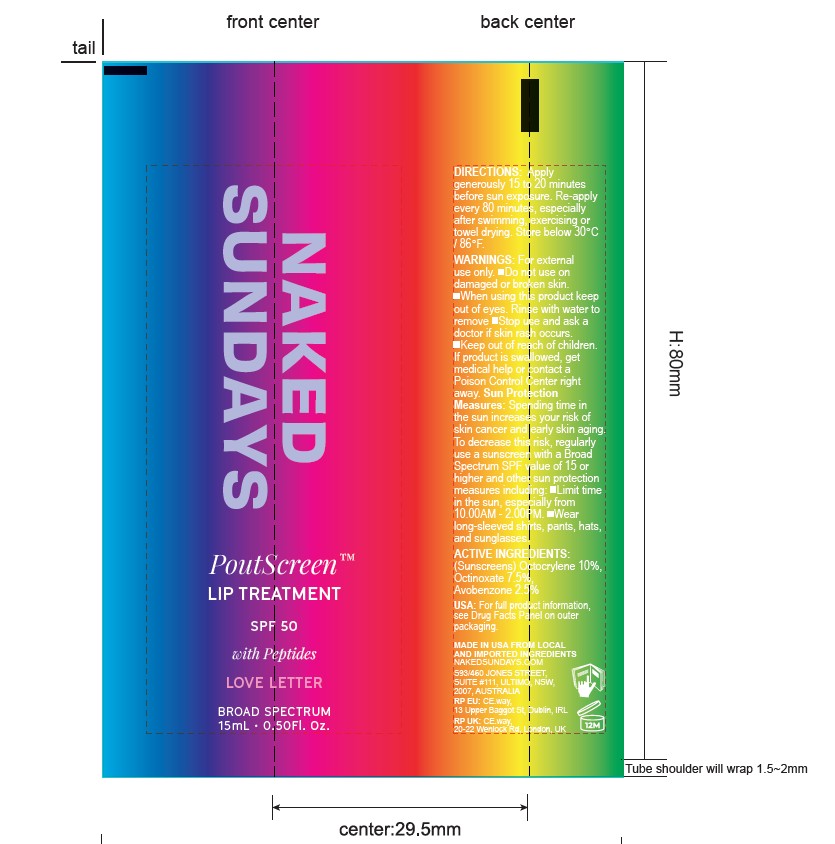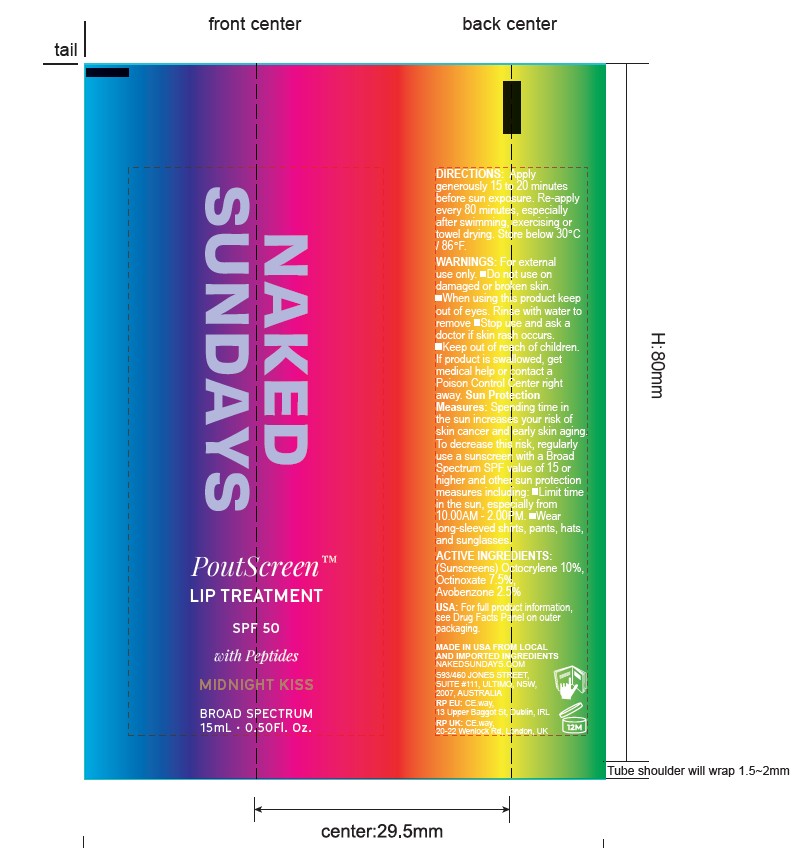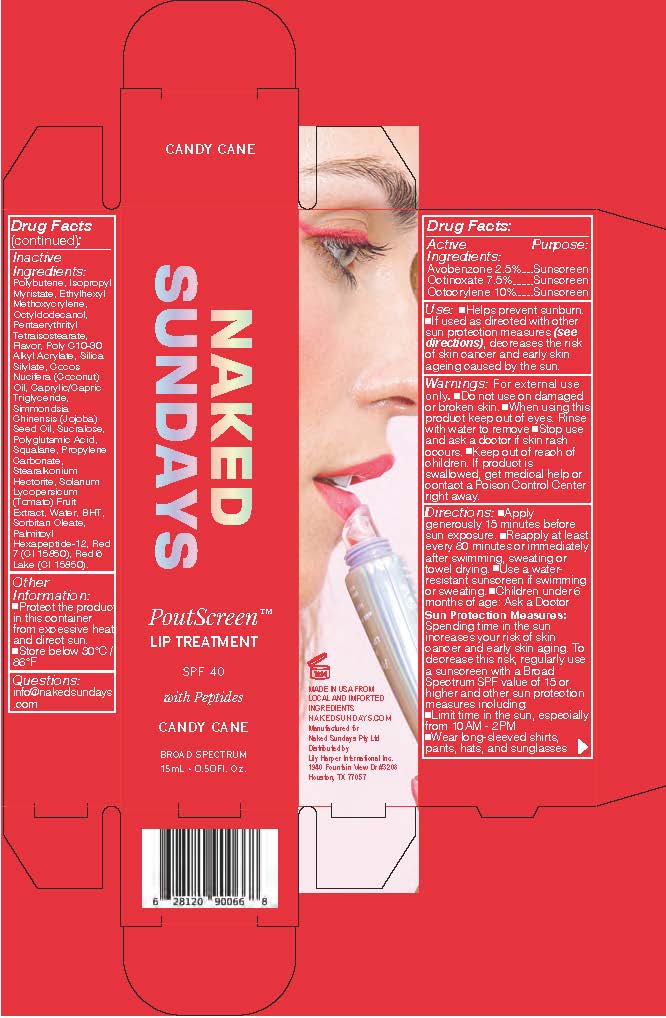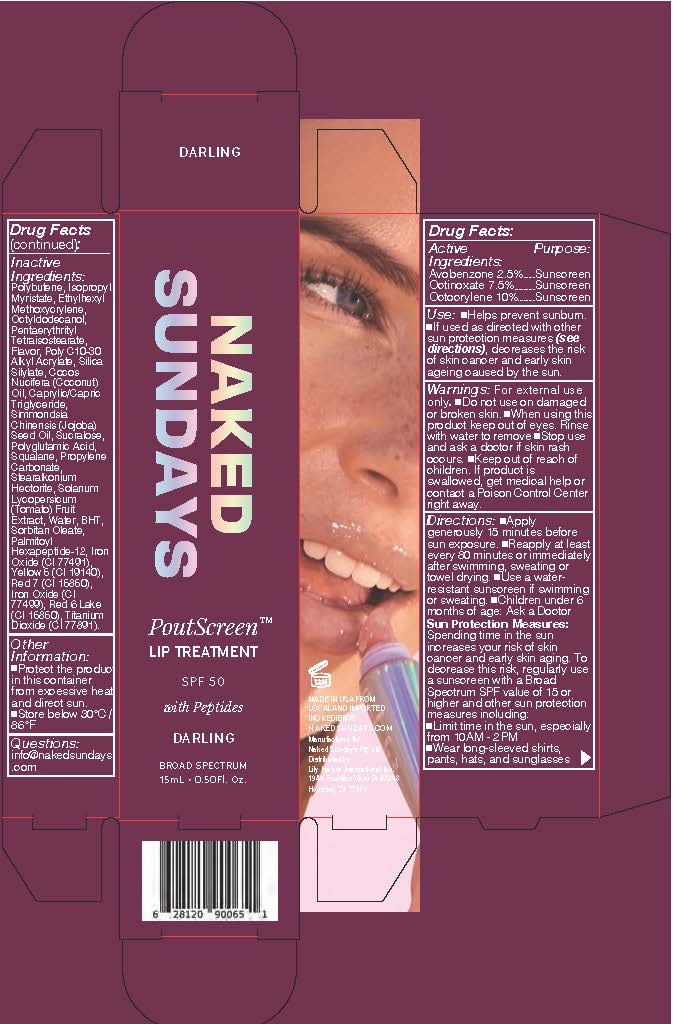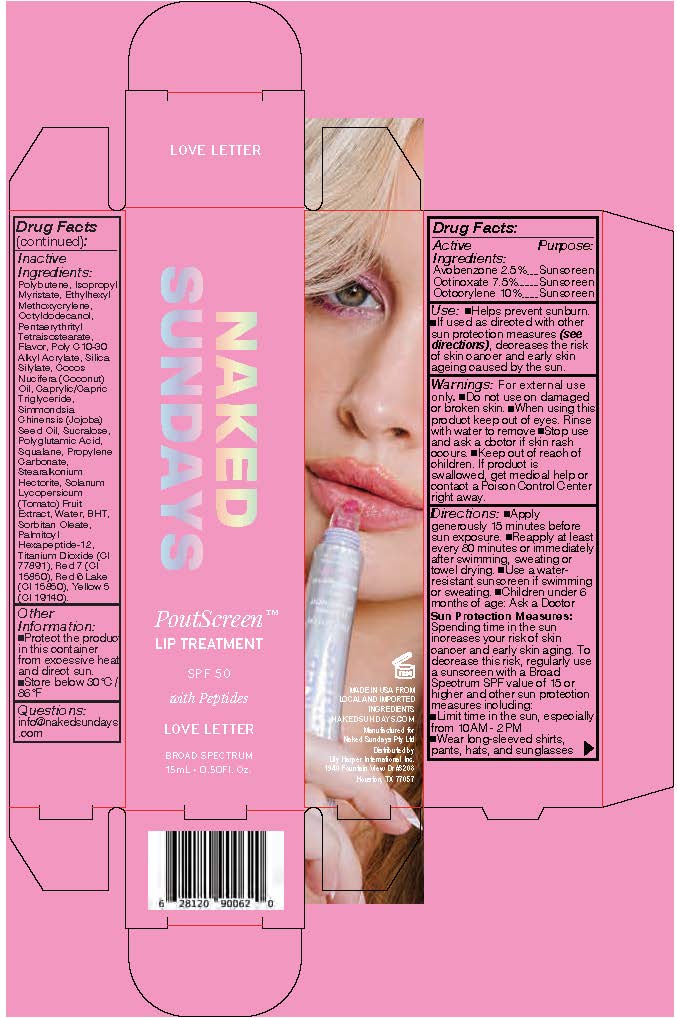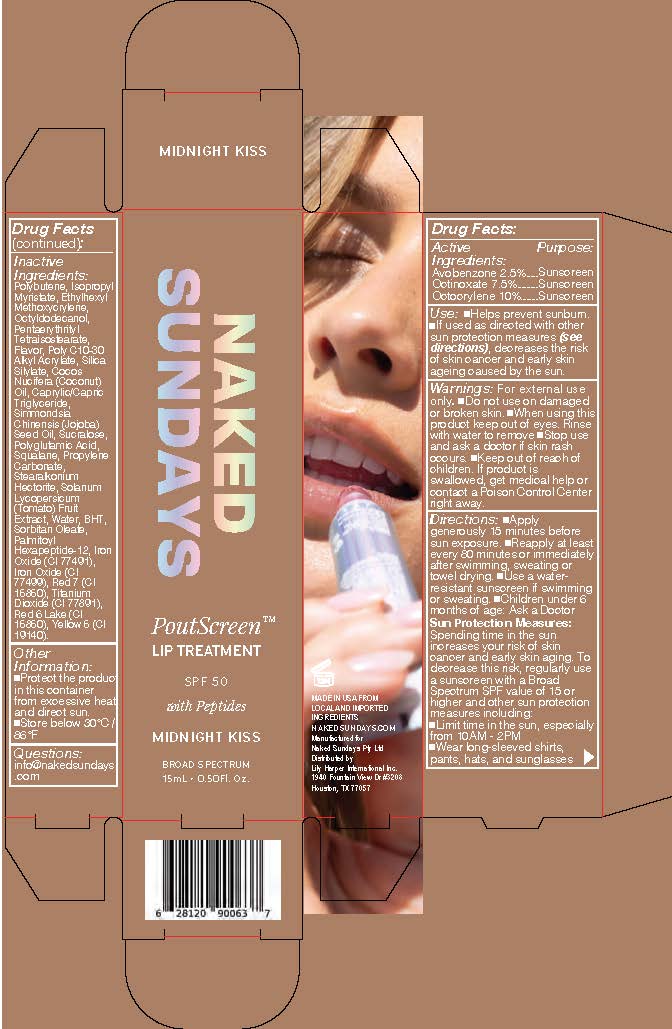 DRUG LABEL: PoutScreen Lip Treatment Midnight Kiss
NDC: 81104-596 | Form: LIQUID
Manufacturer: NAKED SUNDAYS PTY LTD
Category: otc | Type: HUMAN OTC DRUG LABEL
Date: 20260106

ACTIVE INGREDIENTS: OCTINOXATE 7.5 g/100 mL; AVOBENZONE 2.5 g/100 mL; OCTOCRYLENE 10 g/100 mL
INACTIVE INGREDIENTS: ISOPROPYL MYRISTATE; COCOS NUCIFERA (COCONUT) OIL; STEARALKONIUM HECTORITE; PALMITOYL HEXAPEPTIDE-12; CI 19140; SOLANUM LYCOPERSICUM (TOMATO) FRUIT; POLYGLUTAMIC ACID (1200 MW); SUCRALOSE; WATER; SILICA DIMETHYL SILYLATE; POLYBUTENE (1400 MW); ETHYLHEXYL METHOXYCRYLENE; SORBITAN OLEATE; CI 77891; SQUALANE; PROPYLENE CARBONATE; PENTAERYTHRITYL TETRAISOSTEARATE; OCTYLDODECANOL; BEHENYL ACRYLATE POLYMER; CAPRYLIC/CAPRIC TRIGLYCERIDE; SIMMONDSIA CHINENSIS (JOJOBA) SEED OIL; CI 15850; CI 77491; CI 77499

Poutscreen Lip Treatment

Use:

• Helps prevent sunburn.

• If used as directed with other sun protection measures (see Directions), decreases the risk of skin cancer and early skin ageing caused by the sun

Warnings: For external use only.

• Do not use on damaged or broken skin.

When using this product: Keep out of eyes. Rinse with water to remove.

Stop use and ask a doctor: If rash occurs.

Keep out of reach of children: If product is swallowed, get medical help or contact a Poison Control Center right away

Directions:

• Apply liberally and evenly 15 minutes before sun exposure.

• Re-apply at least every 80 minutes or immediately after swimming, sweating or towel drying.

• Use a water-resistant sunscreen if swimming or sweating.

Children under 6 months of age: Ask a doctor

Sun Protection Measures: Spending time in the sun increases your risk of skin cancer and early skin aging. To decrease this risk, regularly use a sunscreen with a Broad Spectrum SPF value of 15 or higher and other sun protection measures including:

• Limit time in the sun, especially from 10.00AM - 2.00PM

• Wear long-sleeved shirts, pants, hats, and sunglasses

Other Information:

• Protect this product from excess heat and direct sun.

• Store below 30°C / 86°F

Questions:

• info@nakedSundays.com

INACTIVE INGREDIENT

PoutScreen Love Letter

Inactive Ingredients: Polybutene, Isopropyl Myristate, Ethylhexyl Methoxycrylene, Octyldodecanol, Pentaerythrityl Tetraisostearate, Flavor, Poly C10-30 Alkyl Acrylate, Silica Silylate, Cocos Nucifera (Coconut) Oil, Caprylic/Capric Triglyceride, Simmondsia Chinensis (Jojoba) Seed Oil, Sucralose, Polyglutamic Acid, Squalane, Propylene Carbonate, Stearalkonium Hectorite, Solanum Lycopersicum (Tomato) Fruit Extract, Water, BHT, Sorbitan Oleate, Palmitoyl Hexapeptide-12, Titanium Dioxide (CI 77891), Red 7 (CI 15850), Red 6 Lake (CI 15850), Yellow 5 (CI 19140).

PoutScreen Darling

Inactive Ingredients: Polybutene, Isopropyl Myristate, Ethylhexyl Methoxycrylene, Octyldodecanol, Pentaerythrityl Tetraisostearate, Flavor, Poly C10-30 Alkyl Acrylate, Silica Silylate, Cocos Nucifera (Coconut) Oil, Caprylic/Capric Triglyceride, Simmondsia Chinensis (Jojoba) Seed Oil, Sucralose, Polyglutamic Acid, Squalane, Propylene Carbonate, Stearalkonium Hectorite, Solanum Lycopersicum (Tomato) Fruit Extract, Water, BHT, Sorbitan Oleate, Palmitoyl Hexapeptide-12, Iron Oxide (CI 77491), Yellow 5 (CI 19140), Red 7 (CI 15850), Iron Oxide (CI 77499), Red 6 Lake (CI 15850), Titanium Dioxide (CI 77891).

PoutScreen Midnight Kiss

Inactive Ingredients: Polybutene, Isopropyl Myristate, Ethylhexyl Methoxycrylene, Octyldodecanol, Pentaerythrityl Tetraisostearate, Flavor, Poly C10-30 Alkyl Acrylate, Silica Silylate, Cocos Nucifera (Coconut) Oil, Caprylic/Capric Triglyceride, Simmondsia Chinensis (Jojoba) Seed Oil, Sucralose, Polyglutamic Acid, Iron Oxides (CI 77491), Squalane, Propylene Carbonate, Stearalkonium Hectorite, Iron Oxides (CI 77499), Red 7 (CI 15850), Titanium Dioxide (CI 77891), Red 6 Lake (CI 15850), Solanum Lycopersicum (Tomato) Fruit/Leaf/Stem Extract, Water, BHT, Yellow 5 (CI 19140), Sorbitan Oleate, Palmitoyl Hexapeptide-12.

PoutScreen Candy Cane

Inactive Ingredients: Polybutene, Isopropyl Myristate, Ethylhexyl Methoxycrylene, Octyldodecanol, Pentaerythrityl Tetraisostearate, Flavor, Poly C10-30 Alkyl Acrylate, Silica Silylate, Cocos Nucifera (Coconut) Oil, Caprylic/Capric Triglyceride, Simmondsia Chinensis (Jojoba) Seed Oil, Sucralose, Polyglutamic Acid, Squalane, Propylene Carbonate, Stearalkonium Hectorite, Solanum Lycopersicum (Tomato) Fruit Extract, Water, BHT, Sorbitan Oleate, Palmitoyl Hexapeptide-12, Red 7 (CI 15850), Red 6 Lake (CI 15850).

ACTIVE INGREDIENT

PoutScreen Love Letter

Active Ingredients: Avobenzone 2.5% , Octinoxate 7.5%, Octocrylene 10%

PoutScreen Darling

Active Ingredients: Avobenzone 2.5% , Octinoxate 7.5%, Octocrylene 10%

PoutScreen Midnight Kiss

Active Ingredients: Octocrylene 10%, Ethylhexyl Methoxycinnamate 7.5%, Avobenzone 2.5%

PoutScreen Candy Cane

Active Ingredients: Avobenzone 2.5% , Octinoxate 7.5%, Octocrylene 10%

PURPOSE

Sunscreen